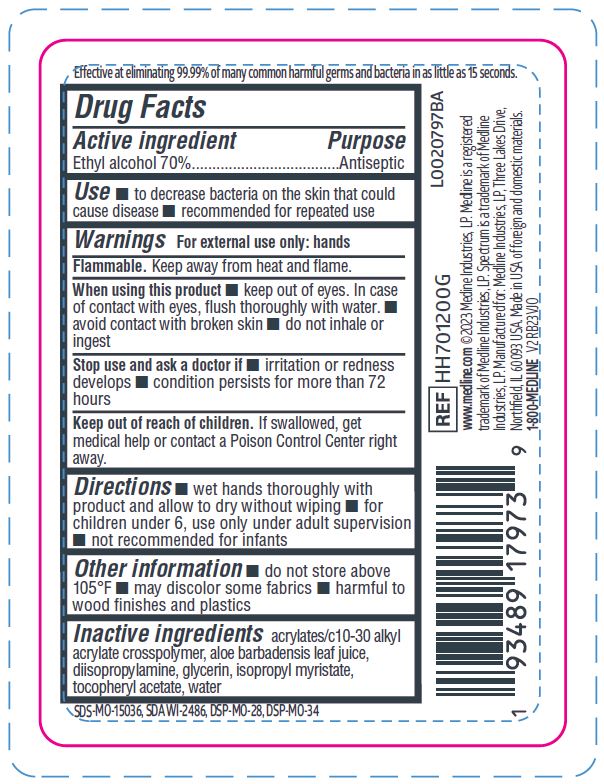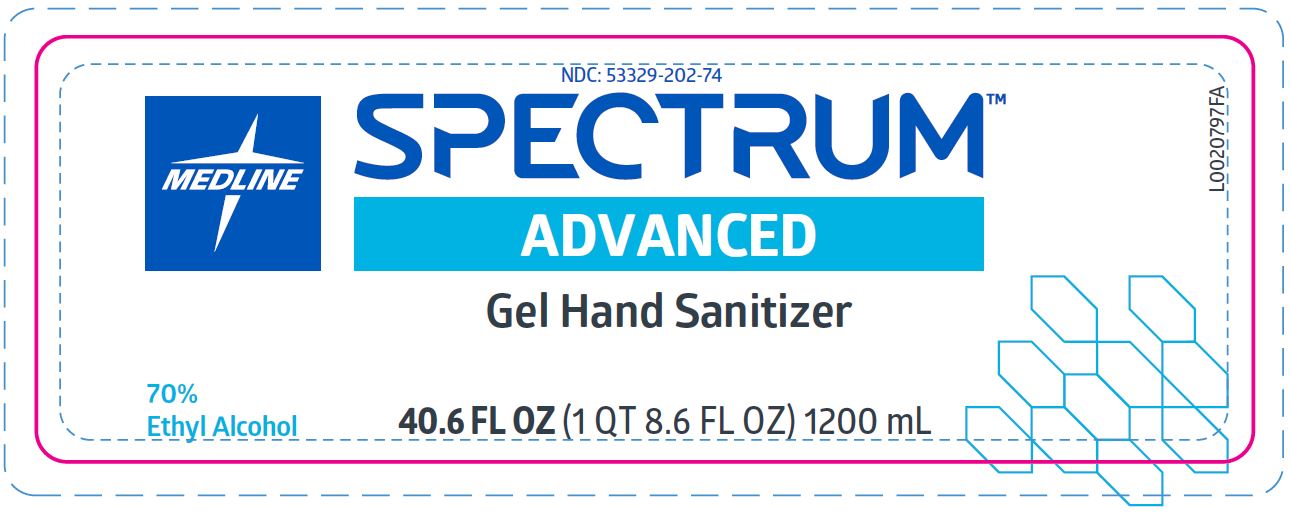 DRUG LABEL: Hand Sanitizer
NDC: 53329-202 | Form: GEL
Manufacturer: Medline Industries, LP
Category: otc | Type: HUMAN OTC DRUG LABEL
Date: 20260211

ACTIVE INGREDIENTS: ALCOHOL 70 mL/100 mL
INACTIVE INGREDIENTS: DIISOPROPYLAMINE; WATER; ALOE VERA LEAF; .ALPHA.-TOCOPHEROL ACETATE, D-; GLYCERIN; ISOPROPYL MYRISTATE; CARBOMER COPOLYMER TYPE B (ALLYL PENTAERYTHRITOL CROSSLINKED)

202 70% Spectrum Advanced Rub

Active ingredient

Ethyl alcohol 70%

Purpose

Antiseptic

Uses

- to decrease bacteria on the skin that could cause disease
- recommended for repeated use

Warnings

For external use only: hands

Flammable. keep away from heat or flame.

When using this product

- keep out of eyes. In case of contact with eyes, flush thoroughly with water
- avoid contact with broken skin
- do not inhale or ingest

Stop use and ask a doctor if

- irritation or redness develop
- condition persists for more than 72 hours

Keep out of reach of children.

If swallowed, get medical help or contact a Poison Control Center right away.

Directions

- wet hands thoroughly with product and allow to dry without wiping
- for children under 6, use only under adult supervision
- not recommended for infants

Other information

- do not store above 105°F
- may discolor some fabrics
- harmful to wood finishes and plastics

Inactive ingredients

acrylates/c10-30 alkyl acrylate crosspolymer, aloe barbadensis leaf juice, diisopropylamine, glycerin, isopropyl myristate, tocopheryl acetate, water

Manufacturing Information

www.medline.com

©2023 Medline Industries, LP.

Medline is a registered trademark of Medline Industries, LP.

Spectrum is a trademark of Medline Industries, LP.

Manufactured for: Medline Industries, LP

Three Lakes Drive, Northfield, IL 60093 USA

Made in USA of foreign and domestic materials.

1-800-MEDLINE

REF: HH701200G

Directions

Added in missing direction for use found on current labeling.